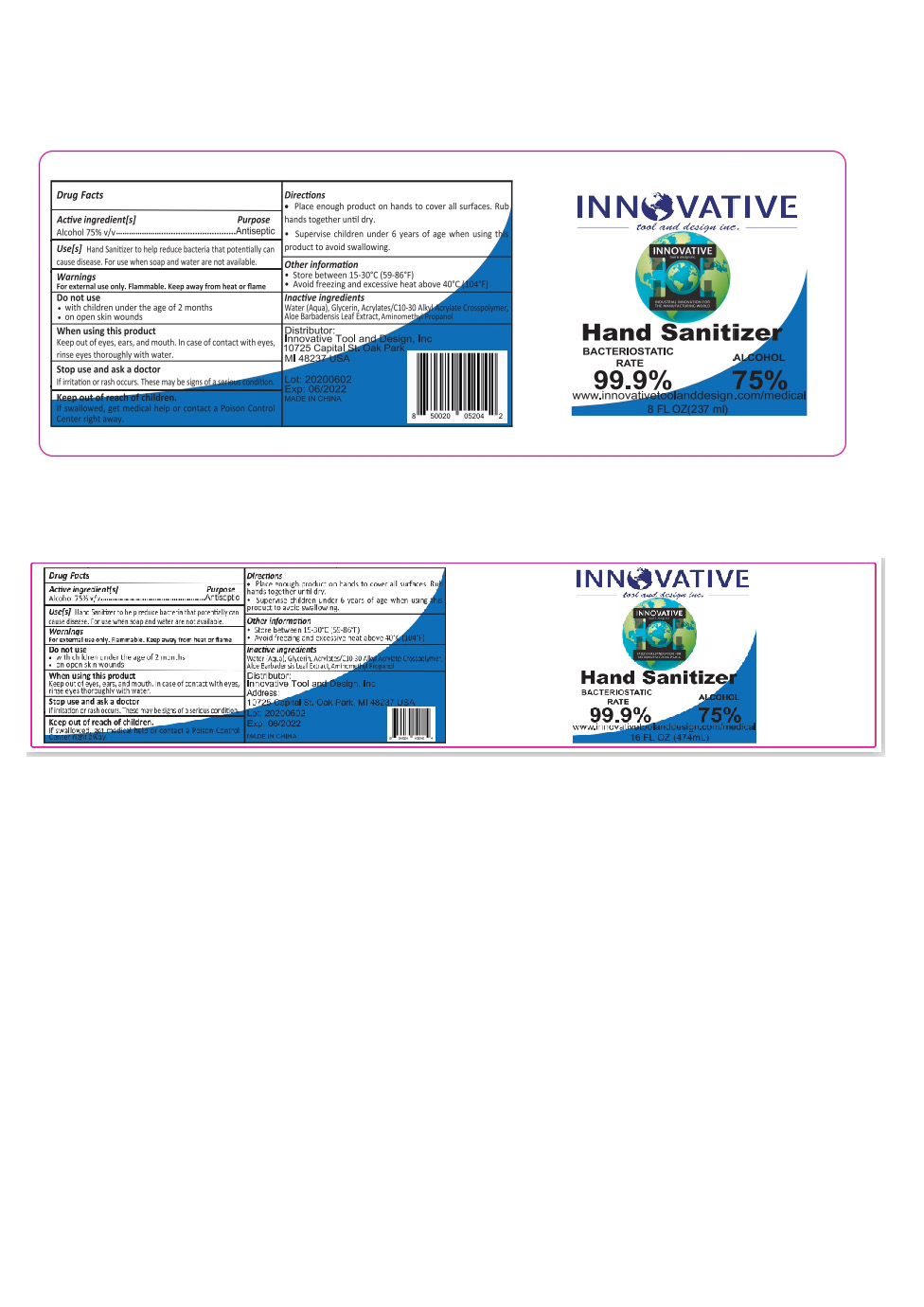 DRUG LABEL: Hand Sanitizer
NDC: 75541-008 | Form: GEL
Manufacturer: Ningbo Meiteli Cosmetic Co., Ltd.
Category: otc | Type: HUMAN OTC DRUG LABEL
Date: 20200615

ACTIVE INGREDIENTS: ALCOHOL 75 mL/100 mL
INACTIVE INGREDIENTS: AMINOMETHYLPROPANOL; GLYCERIN; WATER; ALOE VERA LEAF; CARBOMER COPOLYMER TYPE A (ALLYL PENTAERYTHRITOL CROSSLINKED)

Hand Sanitizer

Active Ingredient(s)

Ethyl Alcohol 75% v/v

Purpose

Antimicrobial

Use

Hand Sanitizer to help reduce bacteria on the skin.

Warning

Flammable. Keep away from heat or flame

For external use only.

Do not use near eyes

In case of contact rinse eyes thoroughly with water.

Stop use

Stop use and see a doctor if imtation or rash appears and lasts

Keep out of reach of children. If swallowed, get medical help or contact a poison control Center right away.

Directions

Place enough product in your palm and rub hands together briskly until dry
Supervise children under 6 years of age should be supervised when using this product to avoid swallowing

Other

- Store below 110F(43C)
- May discolor some fabrics or surfaces

Inactive ingredients

Water(Aqua), Glycerin, Acrylates/C10-30 Alkyl Acrylate Crosspolymer, Aloe Barbadensis Leaf Extract, Aminomethyl Propanol